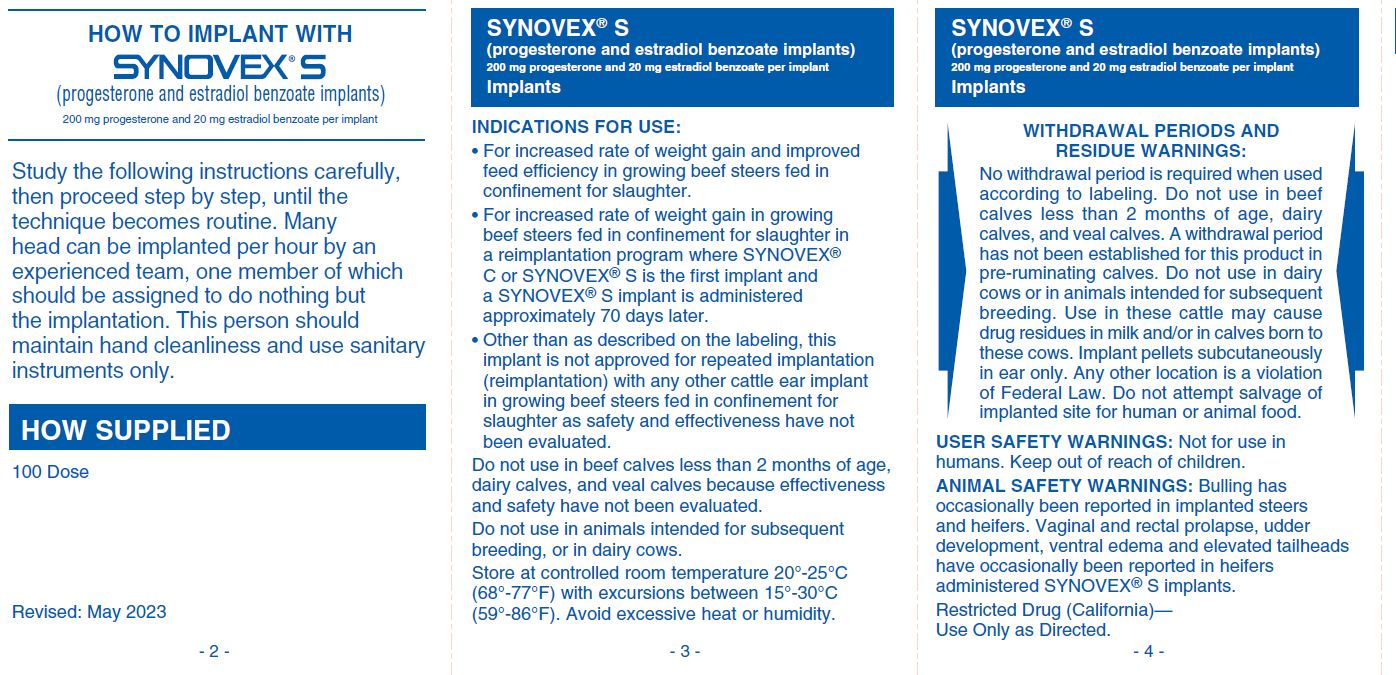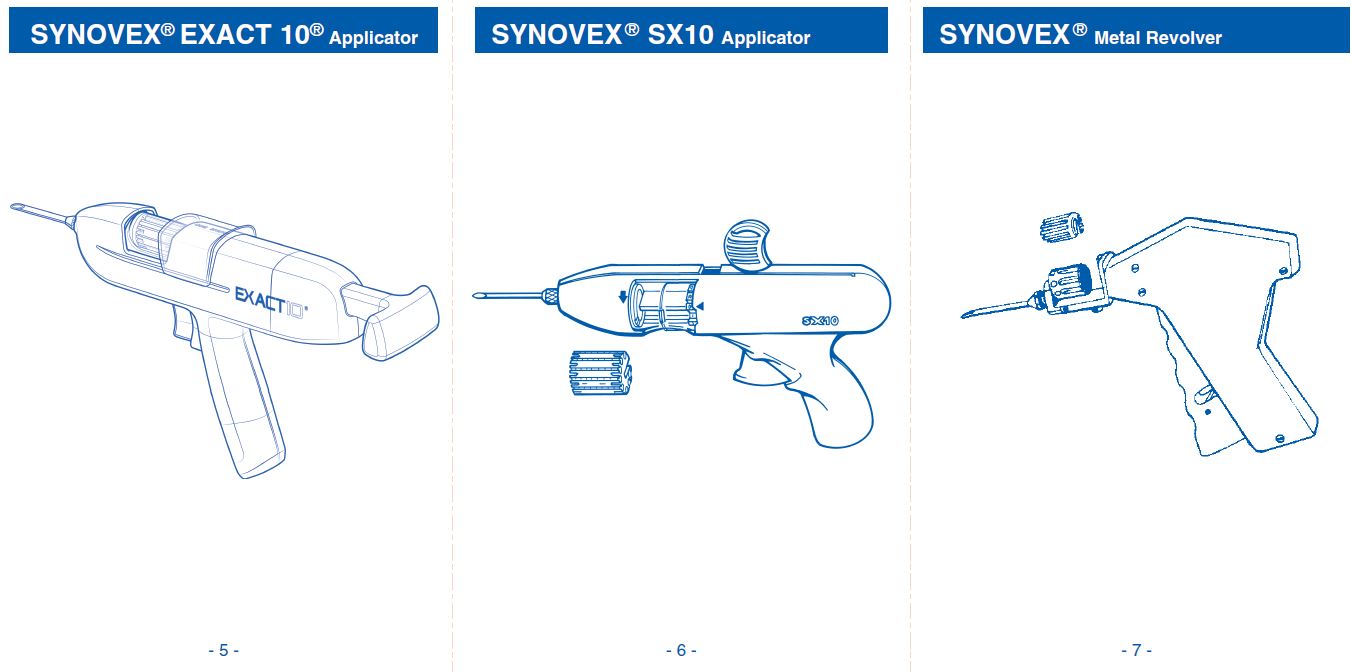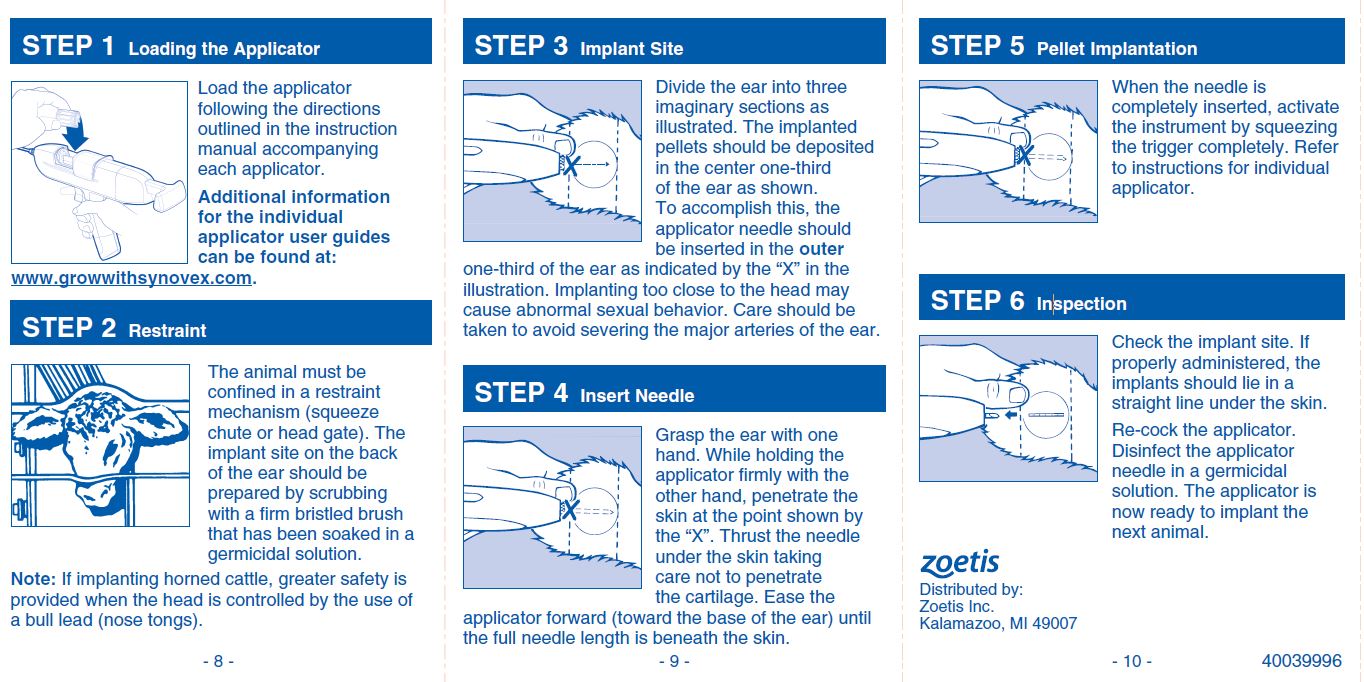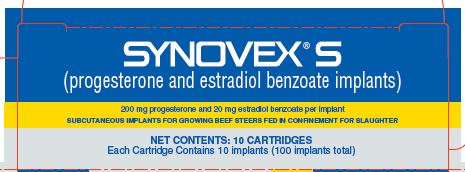 DRUG LABEL: Synovex
NDC: 54771-3902 | Form: IMPLANT
Manufacturer: Zoetis Inc.
Category: animal | Type: OTC ANIMAL DRUG LABEL
Date: 20230706

ACTIVE INGREDIENTS: PROGESTERONE 200 mg/1 1; ESTRADIOL BENZOATE 20 mg/1 1

Synovex® S

Synovex® S
(progesterone and estradiol benzoate implants)
200 mg progesterone and 20 mg estradiol benzoate per implant
SUBCUTANEOUS IMPLANTS FOR GROWING BEEF STEERS FED IN CONFINEMENT FOR SLAUGHTER
This product was manufactured by a non-sterilizing process.
TAKE TIME OBSERVE LABEL DIRECTIONS
Important: Read ALL sides of carton
For subcutaneous ear implantation only.
Approved by FDA under NADA # 009-576
Restricted Drug (California) — Use Only as Directed

WITHDRAWAL PERIODS AND RESIDUE WARNINGS

No withdrawal period is required when used according to labeling. Do not use in beef calves less than 2 months of age, dairy calves, and veal calves. A withdrawal period has not been established for this product in pre-ruminating calves. Do not use in dairy cows or in animals intended for subsequent breeding. Use in these cattle may cause drug residues in milk and/or in calves born to these cows. Implant pellets subcutaneously in ear only. Any other location is a violation of Federal Law. Do not attempt salvage of implanted site for human or animal food.

USER SAFETY WARNINGS

Not for use in humans. Keep out of reach of children.

ANIMAL SAFETY WARNINGS

Bulling has occasionally been reported in implanted steers and heifers. Vaginal and rectal prolapse, udder development, ventral edema and elevated tailheads have occasionally been reported in heifers administered SYNOVEX® S implants.

DIRECTIONS

Implant complete contents of one cartridge cell per steer. Approved implantation technique is fully described in the package insert.
NOTE: Never sacrifice careful, clean technique for speed of implantation.

INDICATIONS FOR USE

• For increased rate of weight gain and improved feed efficiency in growing beef steers fed in confinement for slaughter.
• For increased rate of weight gain in growing beef steers fed in confinement for slaughter in a reimplantation program where SYNOVEX® C or SYNOVEX® S is the first implant and a SYNOVEX® S implant is administered approximately 70 days later.
• Other than as described on the labeling, this implant is not approved for repeated implantation (reimplantation) with any other cattle ear implant in growing beef steers fed in confinement for slaughter as safety and effectiveness have not been evaluated.
Do not use in beef calves less than 2 months of age, dairy calves, and veal calves because effectiveness and safety have not been evaluated.
Do not use in animals intended for subsequent breeding, or in dairy cows.

Storage

Store at controlled room temperature 20°-25°C (68°-77°F) with excursions between 15°-30°C (59°-86°F). Avoid excessive heat or humidity.

QUESTIONS/COMMENTS?

For a copy of the Safety Data Sheet or to report side effects, contact Zoetis Inc. at 1-888-963-8471. For additional information about reporting side effects for animal drugs, contact FDA at 1-888-FDA-VETS or http://www.fda.gov/reportanimalae.

Distributed by:
Zoetis Inc.
Kalamazoo, MI 49007
NET CONTENTS: 10 CARTRIDGES
Each Cartridge Contains 10 implants (100 implants total)
Revised: May 2023
40039996

PRINCIPAL DISPLAY PANEL - 10 Cartridge Implant Carton

40039996